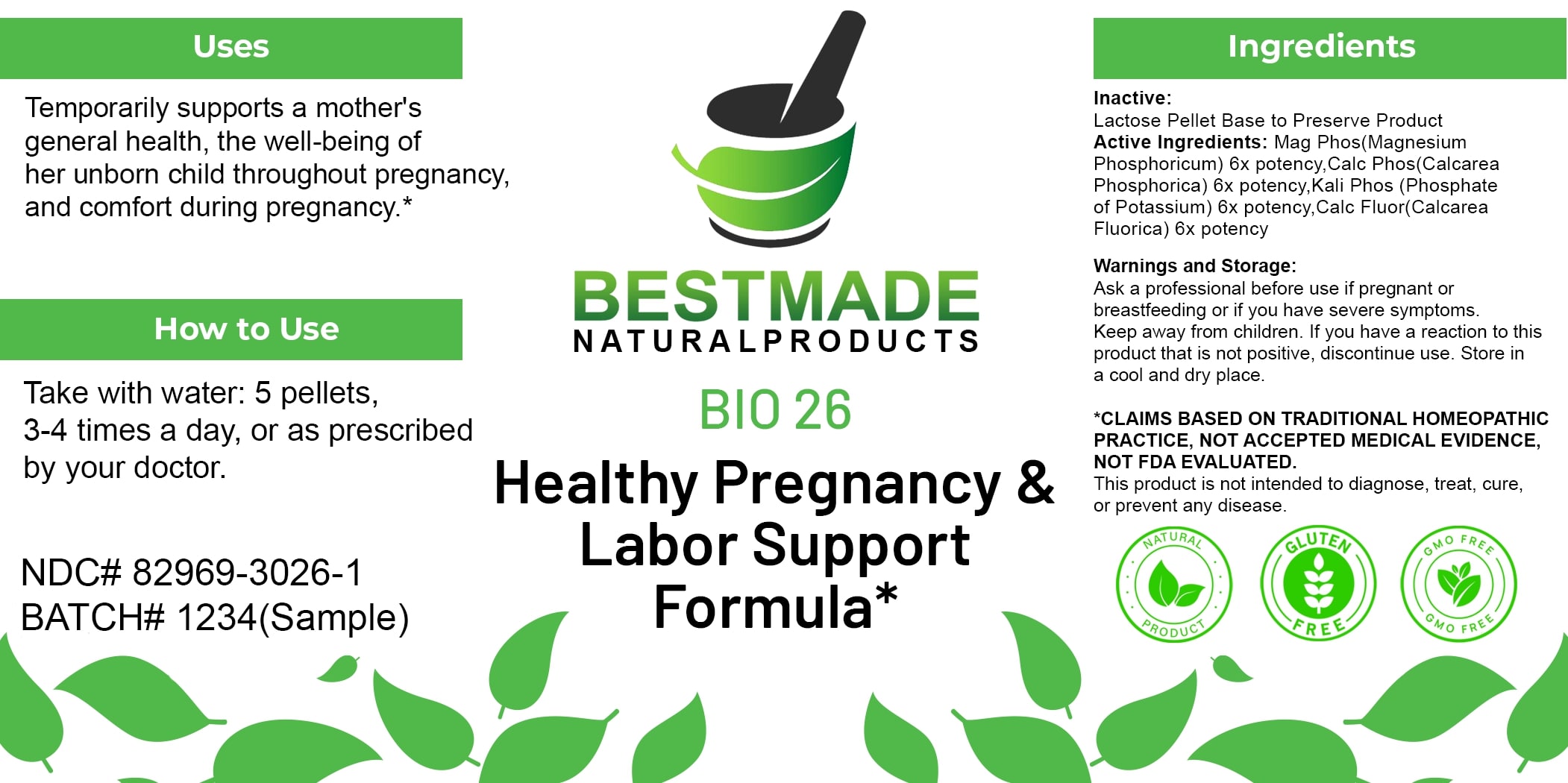 DRUG LABEL: Bestmade Natural Products Bio26
NDC: 82969-3026 | Form: TABLET, SOLUBLE
Manufacturer: Bestmade Natural Products
Category: homeopathic | Type: HUMAN OTC DRUG LABEL
Date: 20250122

ACTIVE INGREDIENTS: CALCIUM FLUORIDE 6 [hp_X]/6 [hp_X]; MAGNESIUM PHOSPHATE, DIBASIC TRIHYDRATE 6 [hp_X]/6 [hp_X]; CALCIUM PHOSPHATE 6 [hp_X]/6 [hp_X]; POTASSIUM PHOSPHATE, UNSPECIFIED FORM 6 [hp_X]/6 [hp_X]
INACTIVE INGREDIENTS: LACTOSE, UNSPECIFIED FORM 6 [hp_X]/6 [hp_X]

BIO26

DOSAGE AND ADMINISTRATION

How to Use

Take with water: 5 pellets, 3-4 times a day, or as prescribed by your doctor.

Uses

Temporarily supports a mother's general health, the well-being of her unborn child throughout pregnancy, and comfort during pregnancy.*

*CLAIMS BASED ON TRADITIONAL HOMEOPATHIC PRACTICE, NOT ACCEPTED MEDICAL EVIDENCE. NOT FDA EVALUATED.

This product is not intended to diagnose, treat, cure, or prevent any disease.

Uses

Temporarily supports a mother's general health, the well-being of her unborn child throughout pregnancy, and comfort during pregnancy.*

*CLAIMS BASED ON TRADITIONAL HOMEOPATHIC PRACTICE, NOT ACCEPTED MEDICAL EVIDENCE. NOT FDA EVALUATED.

This product is not intended to diagnose, treat, cure, or prevent any disease.

ACTIVE INGREDIENT

Active Ingredients: Mag Phos (Magnesium Phosphoricum) 6x potency, Calc Phos (Calcarea Phosphorica) 6x potency, Kali Phos (Phosphate of Potassium) 6x potency, Calc Fluor (Calcarea Fluorica) 6x potency

INACTIVE INGREDIENT

Ingredients

Inactive: Lactose Pellet Base to Preserve Product

KEEP OUT OF REACH OF CHILDREN

Warnings and Storage:

Ask a professional before use if pregnant or breastfeeding or if you have severe symptoms. Keep away from children. If you have a reaction to this product that is not positive, discontinue use. Store in a cool and dry place.

Warnings and Storage:

Ask a professional before use if pregnant or breastfeeding or if you have severe symptoms. Keep away from children. If you have a reaction to this product that is not positive, discontinue use. Store in a cool and dry place.

*CLAIMS BASED ON TRADITIONAL HOMEOPATHIC PRACTICE, NOT ACCEPTED MEDICAL EVIDENCE. NOT FDA EVALUATED.

This product is not intended to diagnose, treat, cure, or prevent any disease.

Entire package label